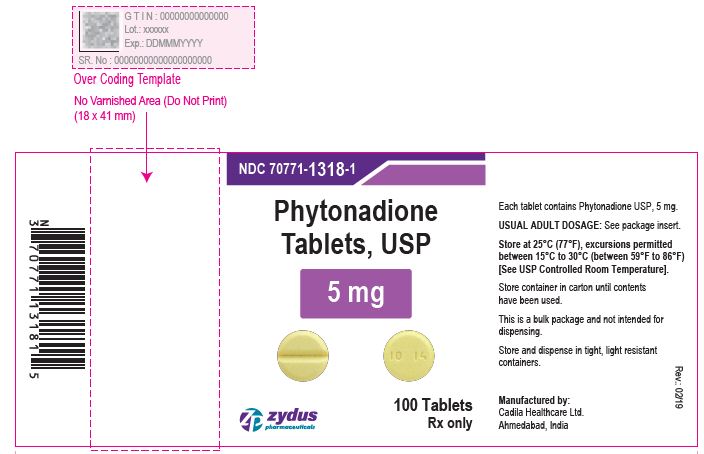 DRUG LABEL: Phytonadione
NDC: 70771-1318 | Form: TABLET
Manufacturer: Zydus Lifesciences Limited
Category: prescription | Type: HUMAN PRESCRIPTION DRUG LABEL
Date: 20221101

ACTIVE INGREDIENTS: PHYTONADIONE 5 mg/1 1
INACTIVE INGREDIENTS: CELLULOSE, MICROCRYSTALLINE; CROSCARMELLOSE SODIUM; HYDROXYPROPYL CELLULOSE (110000 WAMW); LACTOSE MONOHYDRATE; MAGNESIUM STEARATE; SILICON DIOXIDE

Phytonadione Tablets, USP

PACKAGE LABEL.PRINCIPAL DISPLAY PANEL

Phytonadione Tablets USP, 5 mg

100 tablets

NDC 70771-1318-1

Rx only